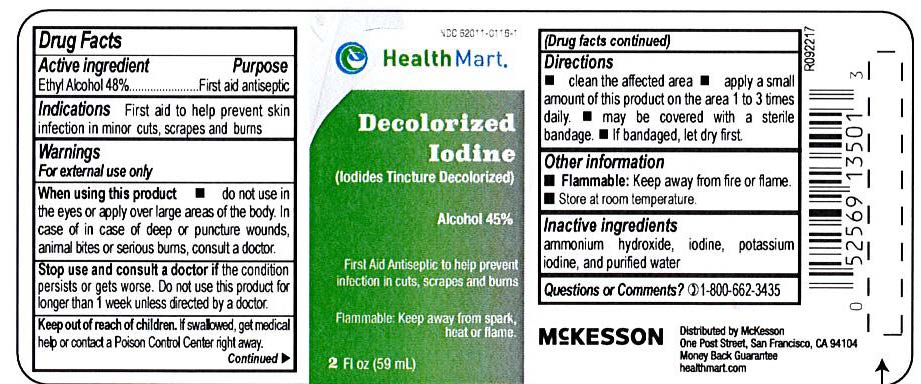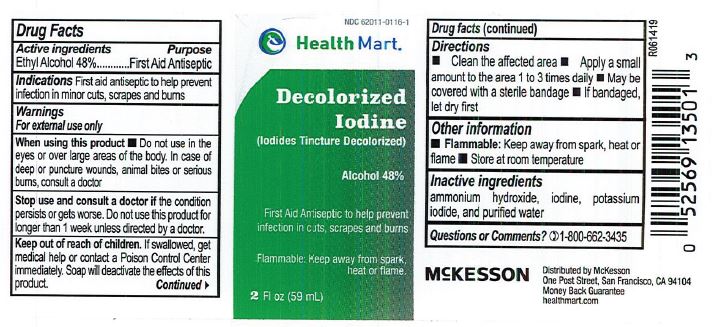 DRUG LABEL: Health Mart Iodides
NDC: 62011-0116 | Form: LIQUID
Manufacturer: Strategic Sourcing Services LLC
Category: otc | Type: HUMAN OTC DRUG LABEL
Date: 20231220

ACTIVE INGREDIENTS: ALCOHOL 0.48 mL/1 mL
INACTIVE INGREDIENTS: AMMONIA; IODINE; POTASSIUM IODIDE; WATER

Health Mart Decolorized Iodine

Health Mart Iodides Tincture

Drug Facts

Active Ingredient

Alcohol 48% v/v

Purpose

Antiseptic

Uses

To help prevent infection in in minor: cuts, scrapes and burns.

Warnings

For external use only

Ask a doctor before use if you have

deep or puncture wounds. Animal bites. Serious burns.

Stop use and consult a doctor if:

Condition persists or gets worse, or if using this product for more than 1 week.

When using this product.

Do not use in the eyes. If contact occurs, flush with large amounts of water while lifting upper and lower lids. Do not apply over large areas of the body.

Keep out of reach of children.

- In case of accidental ingestion, give milk, then a starch solution made by mixing two tablespoons of cornstarch or flour to a pint of water, Contact a Poison Control Center immediately.

Directions

- Clean the affected area. Apply a small amount to the affected area 1 to 3 times daily. May be covered with a sterile bandage. If bandaged, let dry first.

Inactive Ingredient

Ammonia, iodine, potassium iodide, purified water.

Other information

Will stain skin and clothing

Flammable

Keep away from spark, heat and flame